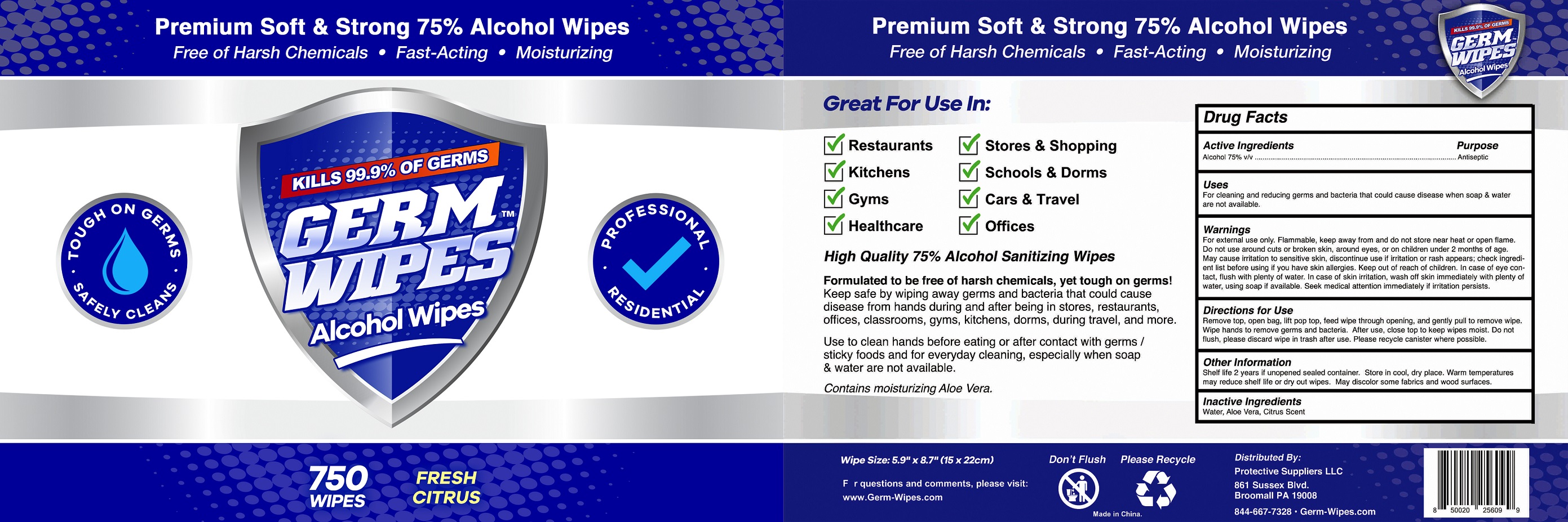 DRUG LABEL: Germ Wipes
NDC: 75662-750 | Form: CLOTH
Manufacturer: Ningbo Chenxing Daily Necessities Co., Ltd.
Category: otc | Type: HUMAN OTC DRUG LABEL
Date: 20200813

ACTIVE INGREDIENTS: ALCOHOL 75 mL/100 g
INACTIVE INGREDIENTS: ALOE VERA LEAF; PECTIN, CITRUS; WATER

75662-750 Germ Wipes /75% Alcoho wipes Ningbo Chenxing Daily Necessities Co., Ltd.

Active Ingredient(s)

Alcohol 75% v/v. Purpose: Antiseptic

Purpose

Antiseptic, Alcohol Wet Wipes

Use

For cleaning and reducing germs and bacteria that could cause disease when soap & water are not available.

Warnings

For external use only. Flammable. Keep away from and do not store near heat or open flame.Do not use around cuts or broken skin, around eyes, or on children under 2 months of age. May cause irritation to sensitive skin,discontinue use if irritation or rash appears; check ingredient list before using if you have skin allergies. Keep out of reach of children. In case of eye contact, flush with plenty of water, In case of skin irritation. wash off skin immediately with plenty of water, using soap if available. Seek medical attention immediately if irritation persists.

Do not use

- in children less than 2 months of age
- on open skin wounds

When using this product keep out of eyes, ears, and mouth. In case of contact with eyes, rinse eyes thoroughly with water.
Stop use and ask a doctor if irritation or rash occurs. These may be signs of a serious condition.
Keep out of reach of children. If swallowed, get medical help or contact a Poison Control Center right away.

Stop use and ask a doctor if irritation or rash occurs. These may be signs of a serious condition.

Keep out of reach of children. If swallowed, get medical help or contact a Poison Control Center right away.

Directions

Remove top, open bag, ,lift pop top,feed wipe through opening, and gently pull to remove wipe. Wipe hands to remove germs and becteria. After use, close top to keep wipes moist. Do not flush, please discard wipe in trash after use. Please recycle canister where possible.

Other information

Shelf life 2 years if unopened sealed container. Store in cool, dry place. Warm temperatures may reduce shelf life or dry out wipes. May discolor some fabrics and wood surface.

Inactive ingredients

Water, Aloe vera, Citrus Scent.

SPL UNCLASSIFIED SECTION

Premium Soft & Strong 75% Alcohol Wipes

Free of Harsh Chemicals, Fast-Acting, Moisturizing

TOUGH ON GERMS, SAFELY CLEANS.

KILLS 99.9% OF GERMS

GERM WIPES

Alcohol Wipes

PROFESSIONAL RESIDENTIAL

750 Wipes

FRESH CITRUS

Great For Use In: Restaurants,Stores & Shopping, Kitchens, Schools & Dorms, Gyms, Cars & Travel, Healthcare, Offices.

High-Quality 75% Alcohol Sanitizing Wipes

Formulated to be free of harsh chemicals, yet tough on germs!

Keep safe by wiping away germs and bacteria that could cause disease from hands during and after being in stores, restaurants, offices, classrooms, gyms, kitchens, dorms, during travel, and more.

Use to clean hands before eating or after contact with germs / sticky foods and for everyday cleaning, especially when soap & water are not available.

Contains moisturizing Aloe Vera.

Package Label - Principal Display Panel

750 Wipes NDC: 75662-750-01